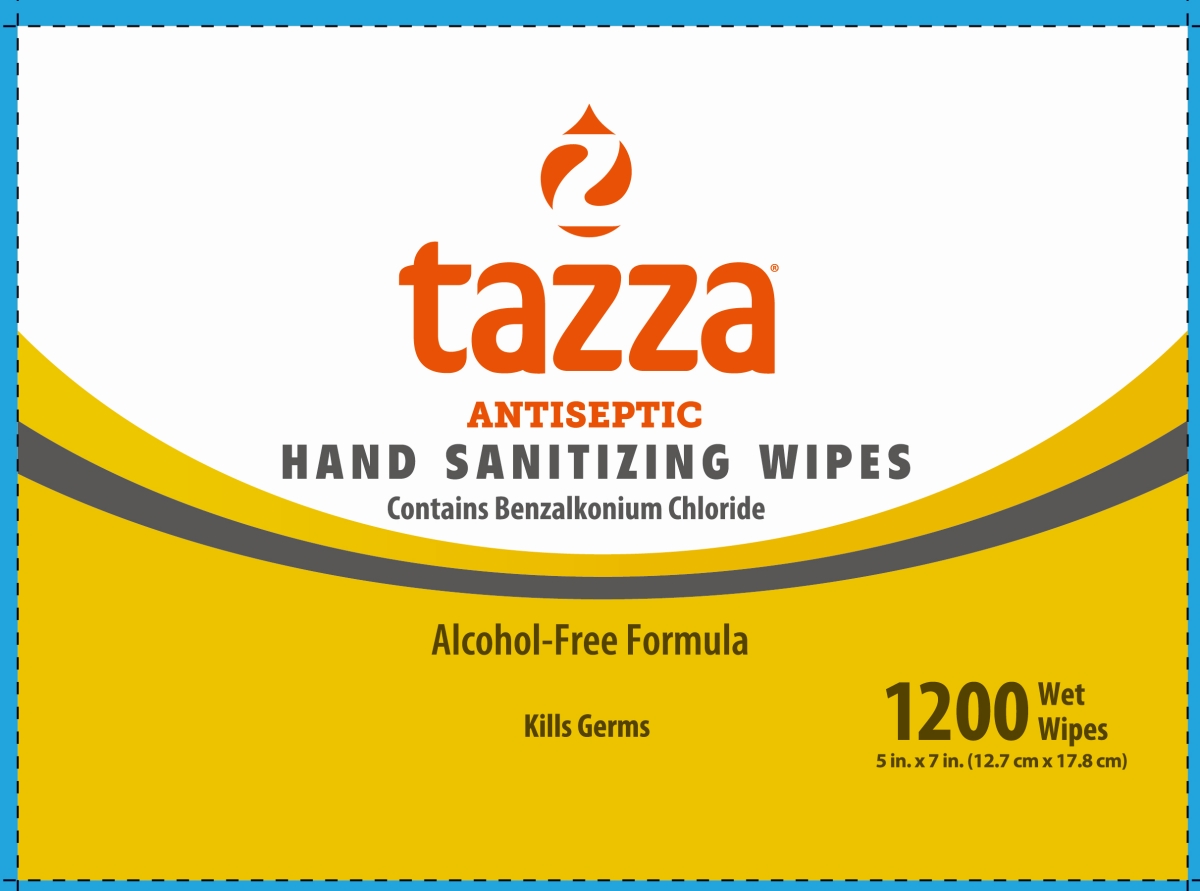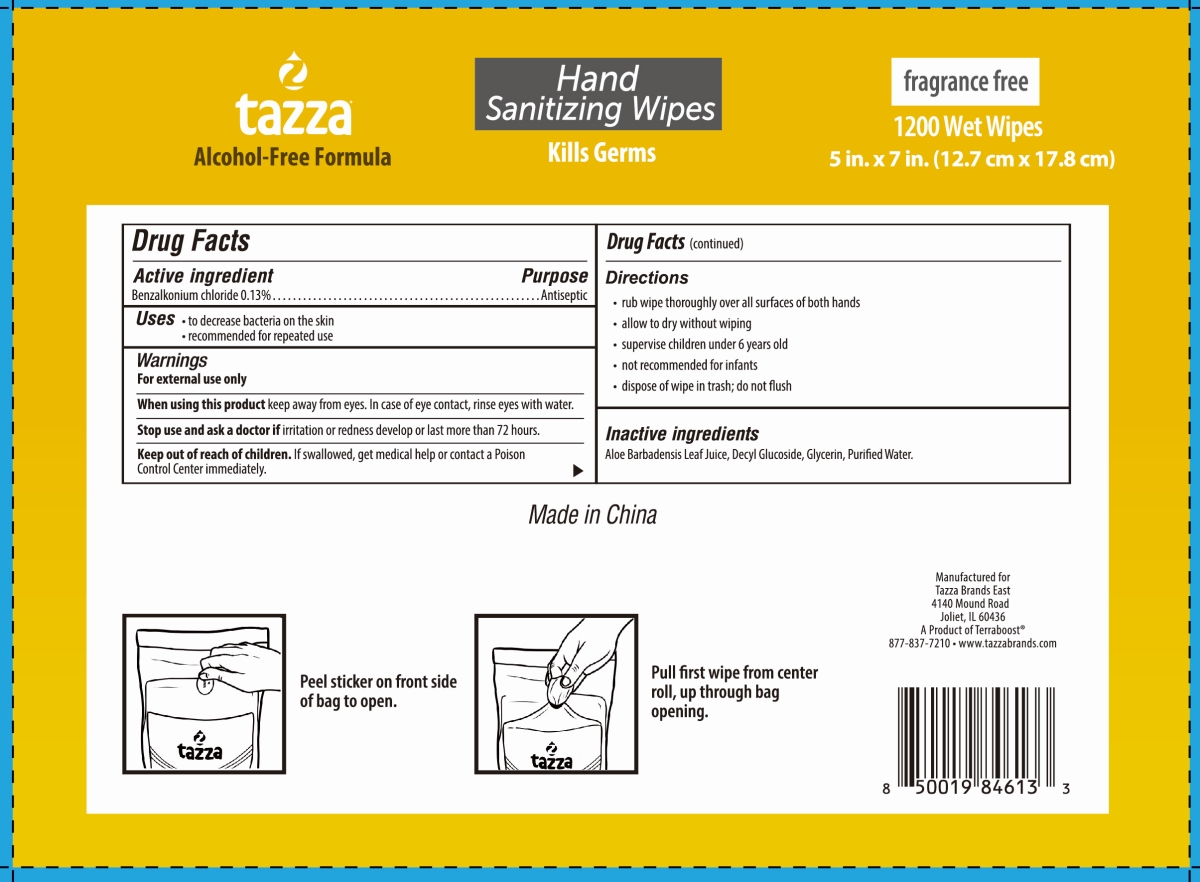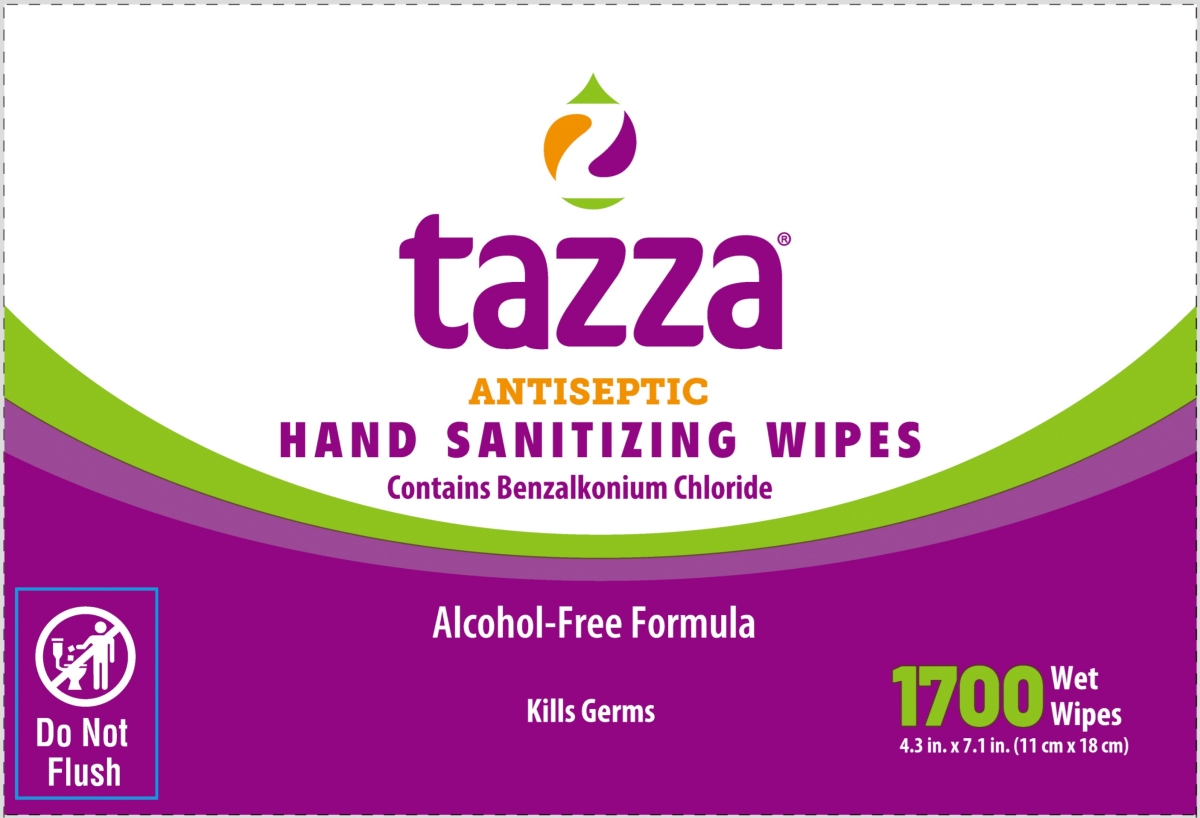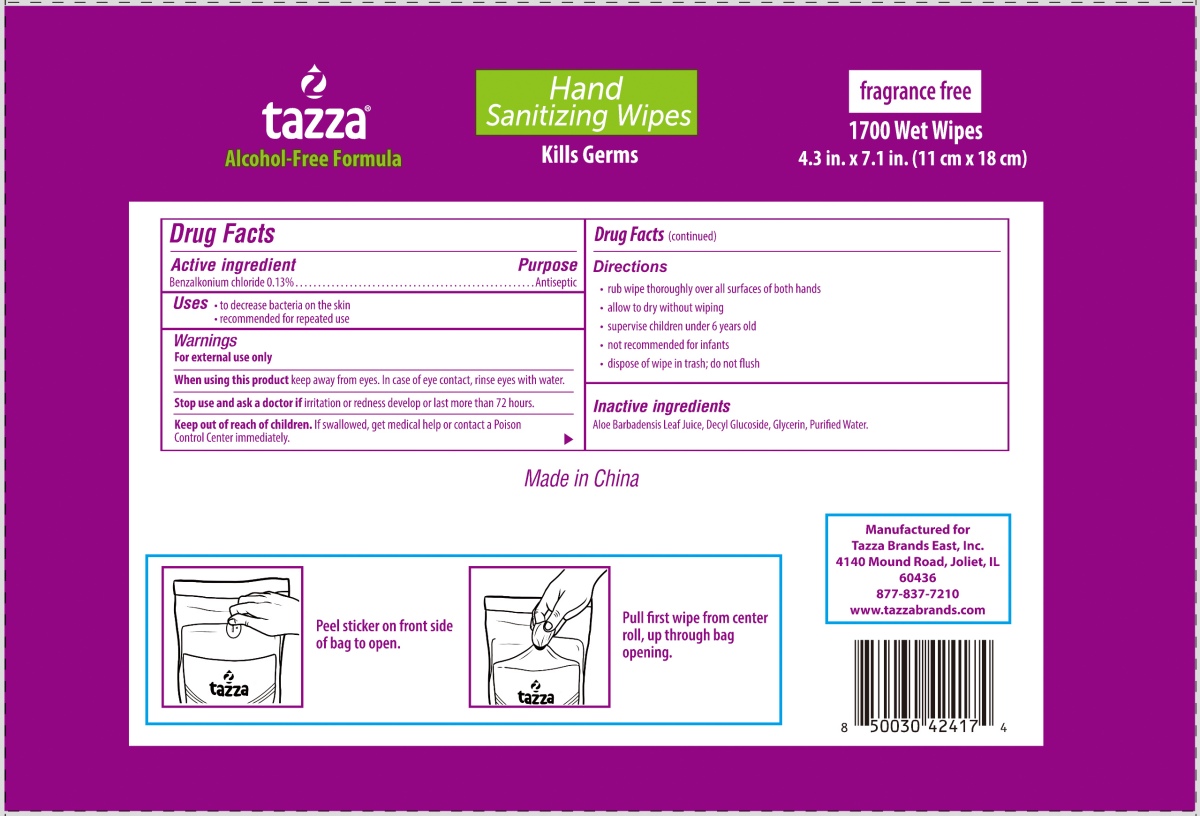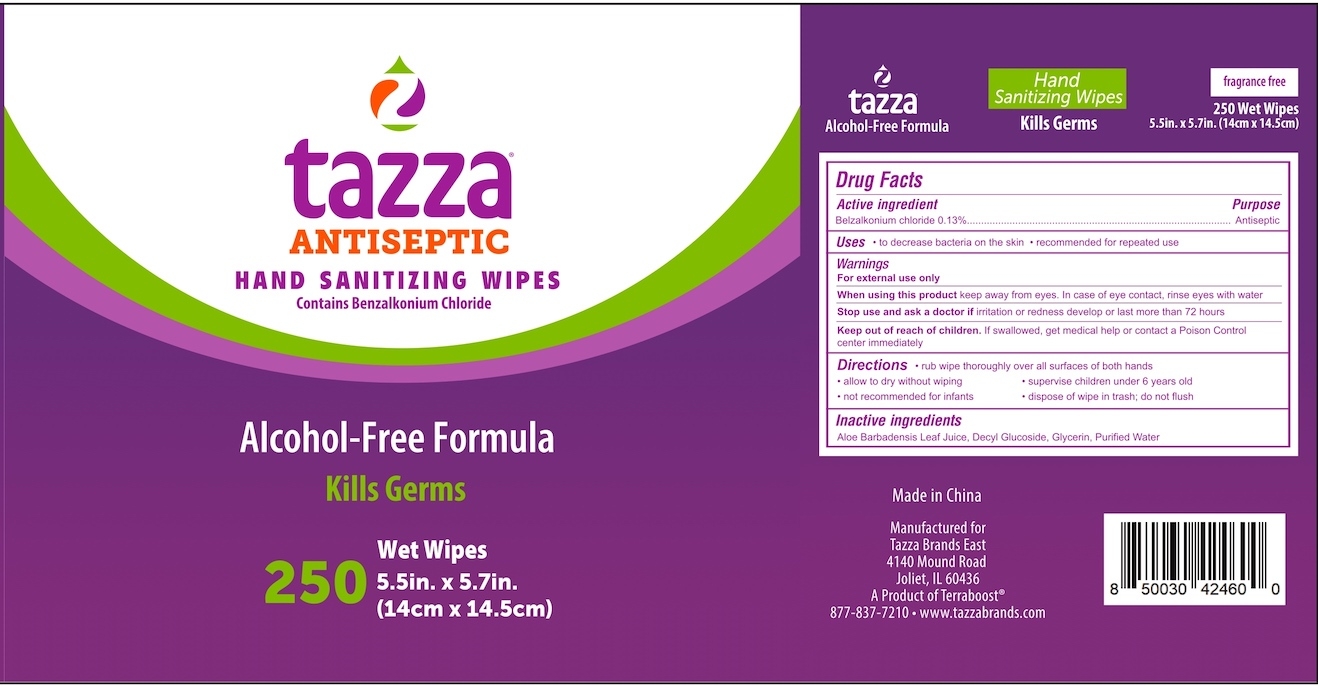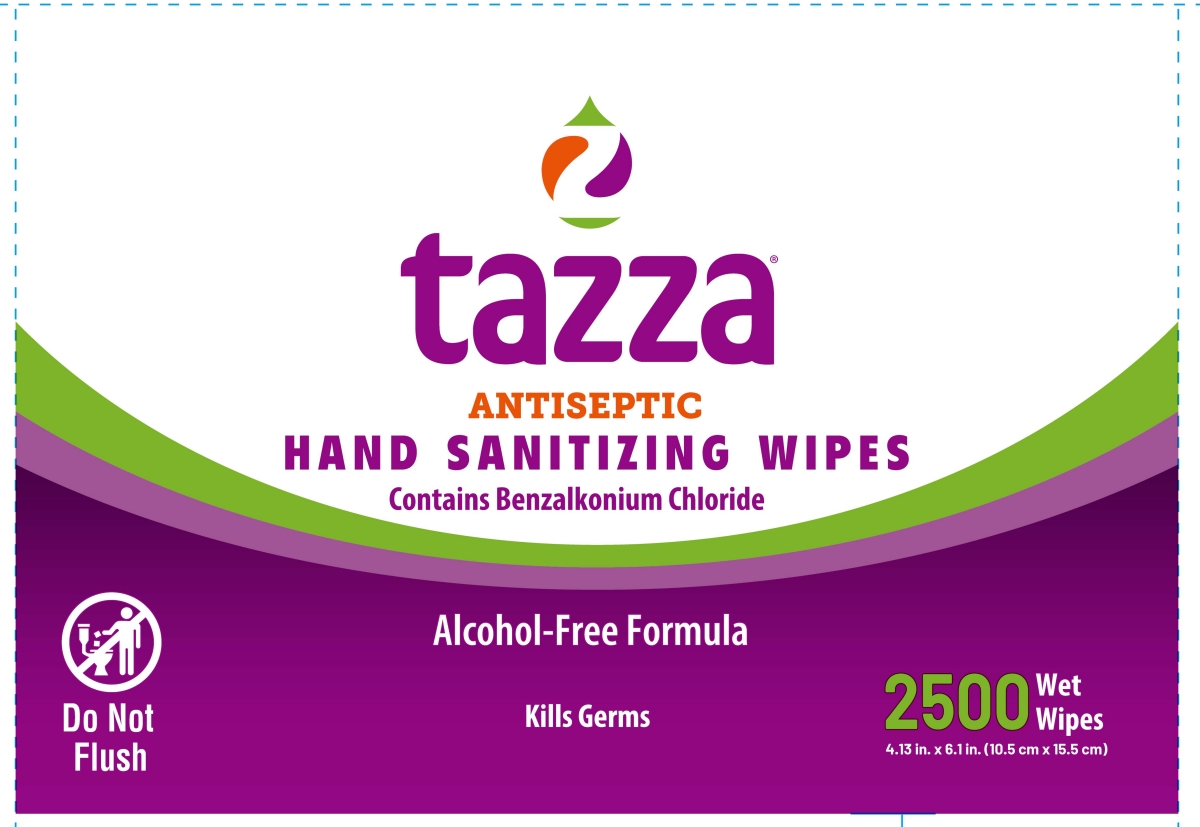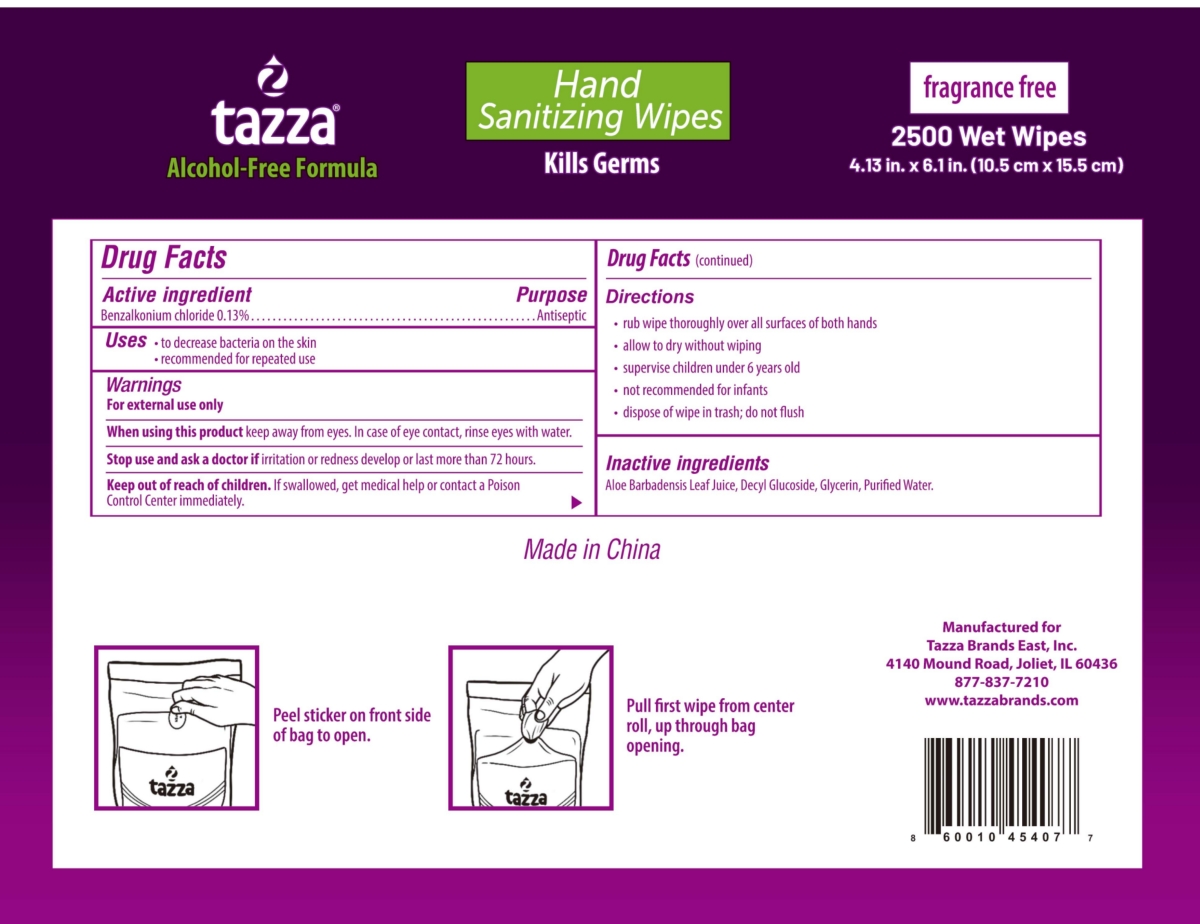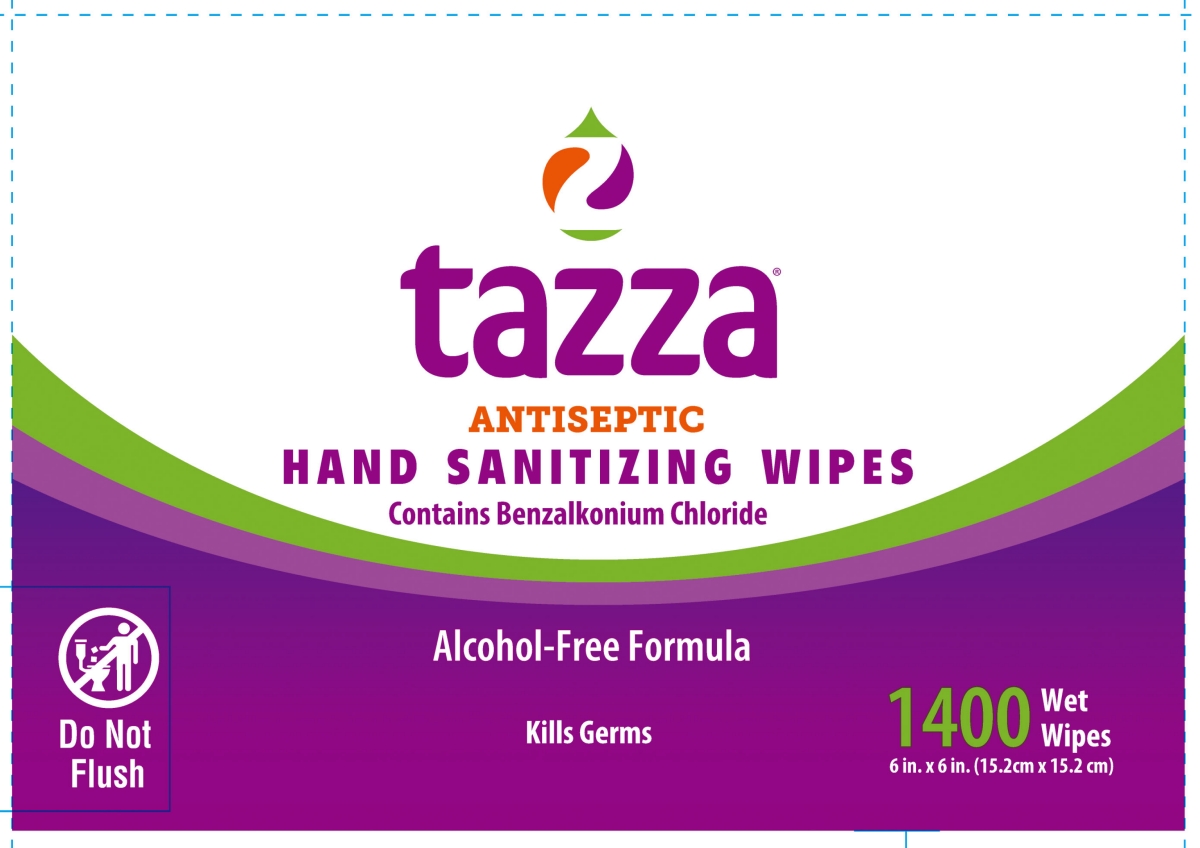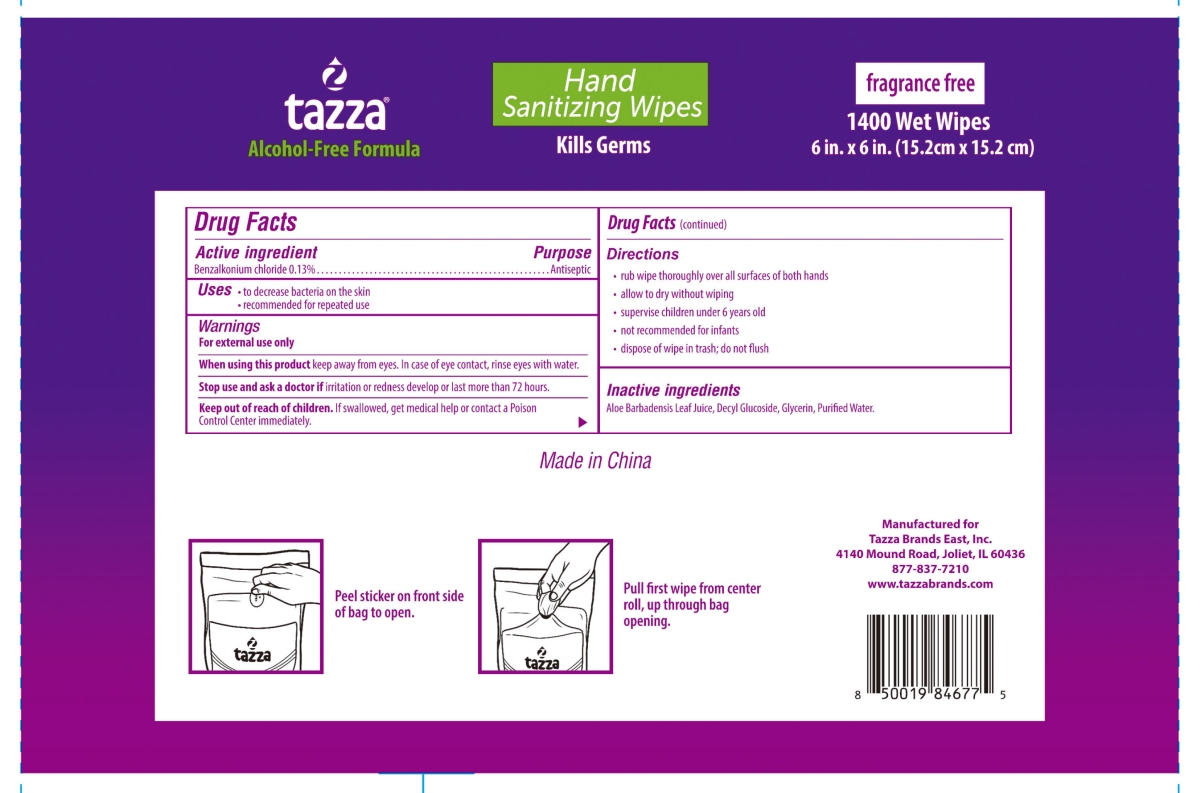 DRUG LABEL: Tazza Antiseptic Hand Sanitizing Wipes
NDC: 76370-0016 | Form: CLOTH
Manufacturer: Tazza Brands East, Inc.
Category: otc | Type: HUMAN OTC DRUG LABEL
Date: 20251218

ACTIVE INGREDIENTS: BENZALKONIUM CHLORIDE 0.13 g/100 mL
INACTIVE INGREDIENTS: GLYCERIN; ALOE VERA LEAF; DECYL GLUCOSIDE; WATER

76370-0016 Tazza Antiseptic Hand Sanitizing Wipes

Drug Facts

Active ingredient

Benzalkonium chloride 0.13%

Purpose

Antiseptic

Uses

- to decrease bacteria on the skin
- recommended for repeated use

Warnings

For external use only

WHEN USING

When using this productkeep away from eyes. In case of eye contact, rinse eyes with water.

Stop use and ask a doctor ifirritation or redness develop or last more than 72 hours.

Keep out of reach of children.If swallowed, get medical help or contact a Poison Control Center right away.

Directions

- rub wipe thoroughly over all surfaces of both hands
- allow to dry without wiping
- supervise children under 6 years old
- not recommended for infants
- dispose of wipe in trash; do not fliush

INACTIVE INGREDIENT

Inactive ingredientsAloe Barbadensis Leaf Juice, Decyl Glucoside, Glycerin, Purified Water.

Made in China

Manufactured for Tazza Brands East, Inc.

4140 Mound Road, Joliet, IL 60436

877-837-7210

www.tazzabrands.com

PACKAGE LABEL

tazza®

ANTISEPTIC HAND SANITIZING WIPES

Contains Benzalkonium Chloride

Alcohol-Free Formula

Kills germs.

1400Wet Wipes

6 in. x 6 in. (15.2 cm x 15.2 cm)

NDC: 76370-0016-0

PACKAGE LABEL

2500 Wet Wipes
4.13 in. x 6.1 in. (10.5 cm x 15.5 cm)
NDC: 76370-0016-1

PACKAGE LABEL

1200 Wet Wipes
5 in. x 7 in. (12.7 cm x 17.8 cm)
NDC: 76370-0016-2

PACKAGE LABEL

1700 Wet Wipes
4.3 in. x 7.1 in. (11 cm x 18 cm)
NDC: 76370-0016-3

PACKAGE LABEL

250 Wet Wipes
5.5in. x 5.7in.
(14cm x 14.5cm)
NDC: 76370-0016-4